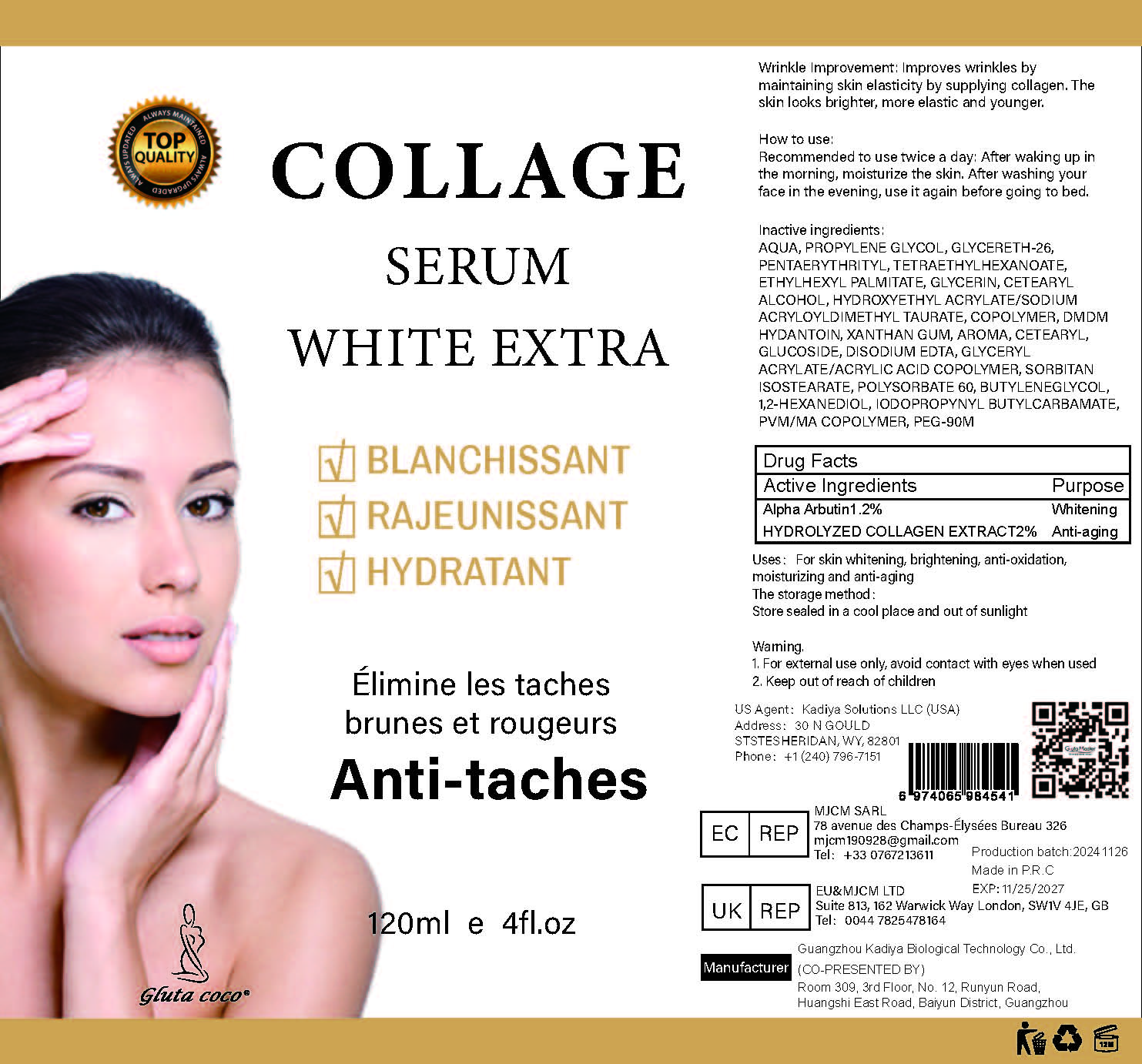 DRUG LABEL: COLLAGE SERUM
NDC: 84423-071 | Form: SOLUTION, CONCENTRATE
Manufacturer: Guangzhou Kadiya Biotechnology Co., Ltd.
Category: otc | Type: HUMAN OTC DRUG LABEL
Date: 20250217

ACTIVE INGREDIENTS: ALPHA-ARBUTIN 1.44 g/120 mL
INACTIVE INGREDIENTS: METHYL VINYL ETHER AND MALEIC ANHYDRIDE COPOLYMER (1100000 WAMW); GLYCERETH-26; DMDM HYDANTOIN; ETHYLHEXYL PALMITATE; PEG-90M; HYDROXYETHYL ACRYLATE/SODIUM ACRYLOYLDIMETHYL TAURATE COPOLYMER (45000 MPA.S AT 1%); SORBITAN ISOSTEARATE; GLYCERIN; EDETATE DISODIUM; GLYCERYL ACRYLATE/ACRYLIC ACID COPOLYMER (300000 CP AT 2%); XANTHAN GUM; 1,3-BUTYLENEGLYCOL DIMETHACRYLATE; AQUA; 1,2-HEXANEDIOL; POLYSORBATE 60; PROPYLENE GLYCOL; IODOPROPYNYL BUTYLCARBAMATE; PENTAERYTHRITYL TETRAETHYLHEXANOATE; CETEARYL ALCOHOL; CETEARYL GLUCOSIDE

PURPOSE

For skin whitening, brightening, anti-oxidation, moisturizing and anti-aging

INACTIVE INGREDIENT

AQUA，PROPYLENE GLYCOL，GLYCERETH-26，PENTAERYTHRITYL，TETRAETHYLHEXANOATE，ETHYLHEXYL PALMITATE，GLYCERIN，CETEARYL ALCOHOL，HYDROXYETHYL ACRYLATE/SODIUM ACRYLOYLDIMETHYL TAURATE，COPOLYMER，DMDM HYDANTOIN，XANTHAN GUM，AROMA，CETEARYL，GLUCOSIDE，DISODIUM EDTA，GLYCERYL ACRYLATE/ACRYLIC ACID COPOLYMER，SORBITAN ISOSTEARATE，POLYSORBATE 60，BUTYLENEGLYCOL，1,2-HEXANEDIOL，IODOPROPYNYL BUTYLCARBAMATE，PVM/MA COPOLYMER，PEG-90M

Warning.
1、For external use only, avoid contact with eyes when used
2、Keep out of reach of children

INDICATIONS AND USAGE

Wrinkle Improvement: Improves wrinkles by maintaining skin elasticity by supplying collagen. The skin looks brighter, more elastic and younger

DOSAGE AND ADMINISTRATION

Recommended to use twice a day: After waking up in the morning, moisturize the skin. After washing vour face in the evening, use it again before going to bed.

KEEP OUT OF REACH OF CHILDREN SECTION

Active Ingredients
Alpha Arbutin1.2%
HYDROLYZED COLLAGEN EXTRACT2%

PACKAGE LABEL

Active Ingredients
Alpha Arbutin1.2%
HYDROLYZED COLLAGEN EXTRACT2%

Uses：
For skin whitening, brightening, anti-oxidation, moisturizing and anti-aging
The storage method：
Store sealed in a cool place and out of sunlight

Warning.
1、For external use only, avoid contact with eyes when used
2、Keep out of reach of children

Inactive ingredients：
AQUA，PROPYLENE GLYCOL，GLYCERETH-26，PENTAERYTHRITYL，TETRAETHYLHEXANOATE，ETHYLHEXYL PALMITATE，GLYCERIN，CETEARYL ALCOHOL，HYDROXYETHYL ACRYLATE/SODIUM ACRYLOYLDIMETHYL TAURATE，COPOLYMER，DMDM HYDANTOIN，XANTHAN GUM，AROMA，CETEARYL，GLUCOSIDE，DISODIUM EDTA，GLYCERYL ACRYLATE/ACRYLIC ACID COPOLYMER，SORBITAN ISOSTEARATE，POLYSORBATE 60，BUTYLENEGLYCOL，1,2-HEXANEDIOL，IODOPROPYNYL BUTYLCARBAMATE，PVM/MA COPOLYMER，PEG-90M